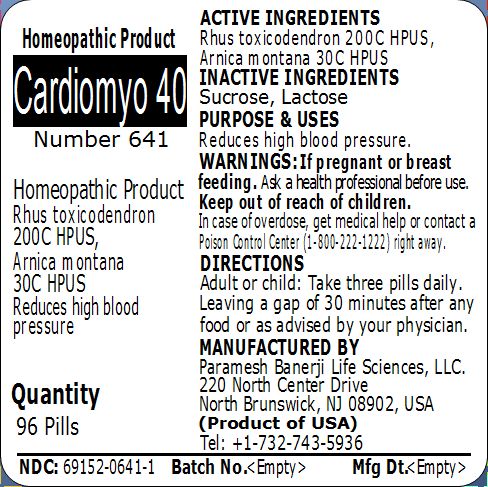 DRUG LABEL: Cardiomyo 40 Number 641
NDC: 69152-0641 | Form: PELLET
Manufacturer: Paramesh Banerji Life Sciences LLC
Category: homeopathic | Type: HUMAN OTC DRUG LABEL
Date: 20150302

ACTIVE INGREDIENTS: TOXICODENDRON PUBESCENS LEAF 200 [hp_C]/1 1; ARNICA MONTANA 30 [hp_C]/1 1
INACTIVE INGREDIENTS: LACTOSE; SUCROSE

Active Ingredients

Rhus toxicodendron 200C HPUS, Arnica montana 30C HPUS

Inactive Ingredients

Sucrose, Lactose

Purpose

Reduces high blood pressure

Uses

Reduces high blood pressure

Warnings

If pregnant or breast feeding ask a health professional before use.

Keep out of reach of children. In case of overdose, get medical help or contact a Poison Control Center (1-800-222-1222) right away.

Direction

Adult or child: Take three pills daily. Leaving a gap of 30 minutes after any food or as advised by your physician.

Manufactured by

Paramesh Banerji Life Sciences, LLC

220 North Center Drive

North Brunswick, NJ 08902, USA

Product of USA

Tel: +1-732-743-5936

Principal Display Panel

Homeopathic Product

Cardiomyo 40

Number 641

Homeopathic Product

Rhus toxicodendron 200C HPUS, Arnica montana 30C HPUS

Reduces high blood pressure

Quantity

96 Pills